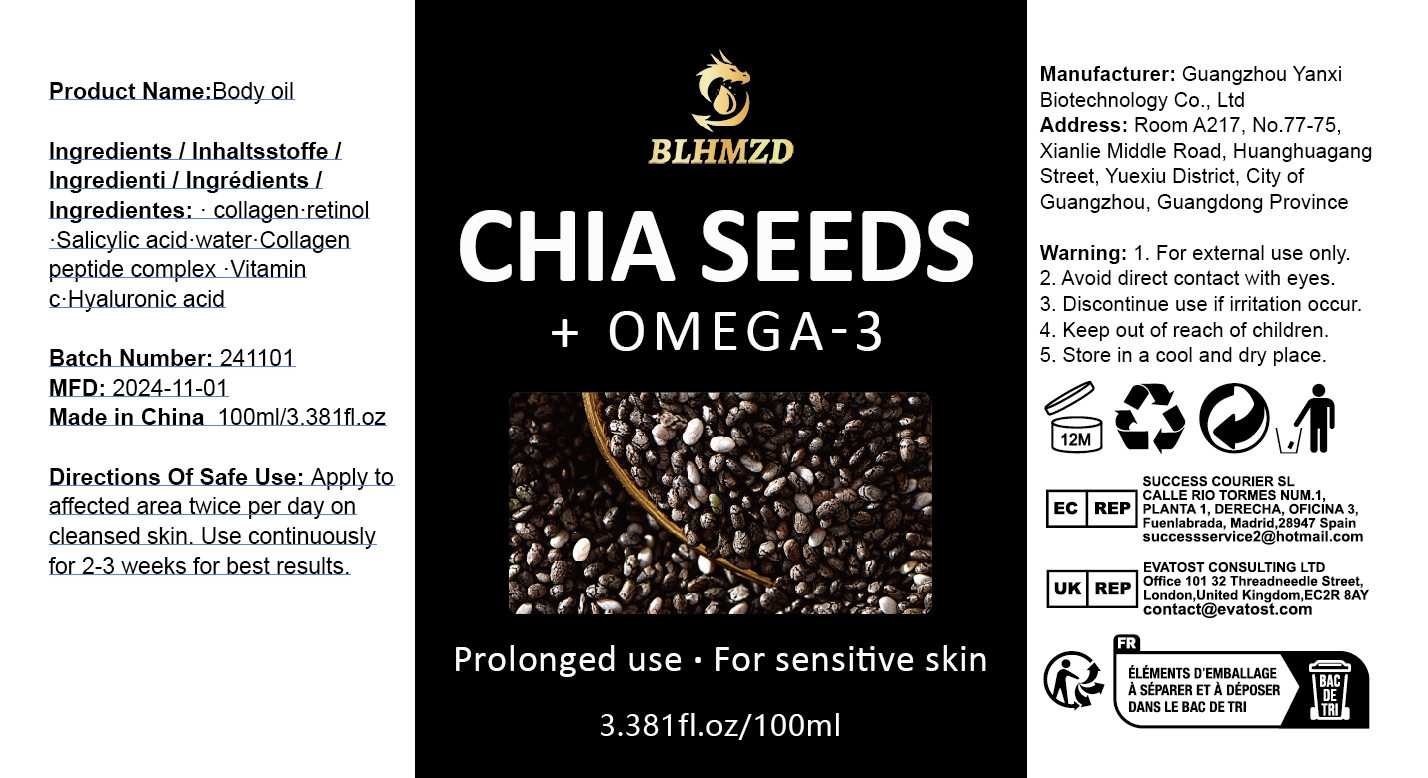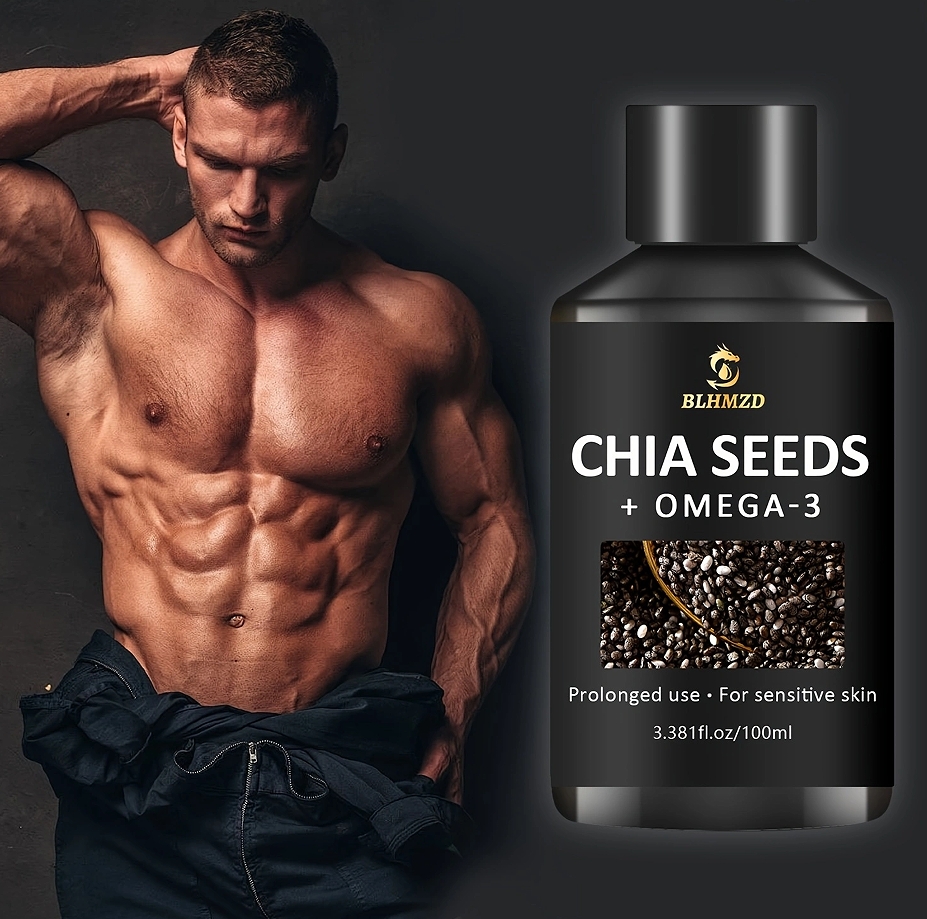 DRUG LABEL: Body oil
NDC: 84025-320 | Form: LIQUID
Manufacturer: Guangzhou Yanxi Biotechnology Co., Ltd
Category: otc | Type: HUMAN OTC DRUG LABEL
Date: 20250110

ACTIVE INGREDIENTS: RETINOL 5 mg/100 mL; HYALURONIC ACID 3 mg/100 mL
INACTIVE INGREDIENTS: WATER

WARNINGS

Keep out of children

DOSAGE AND ADMINISTRATION

Apply to affected area twice per day on cleansed skin.Use continuously for 2-3 weeks for best results.

INACTIVE INGREDIENT

Aqua

INDICATIONS AND USAGE

For daily skin care

Keep out of children

PURPOSE

Moisturizing skin